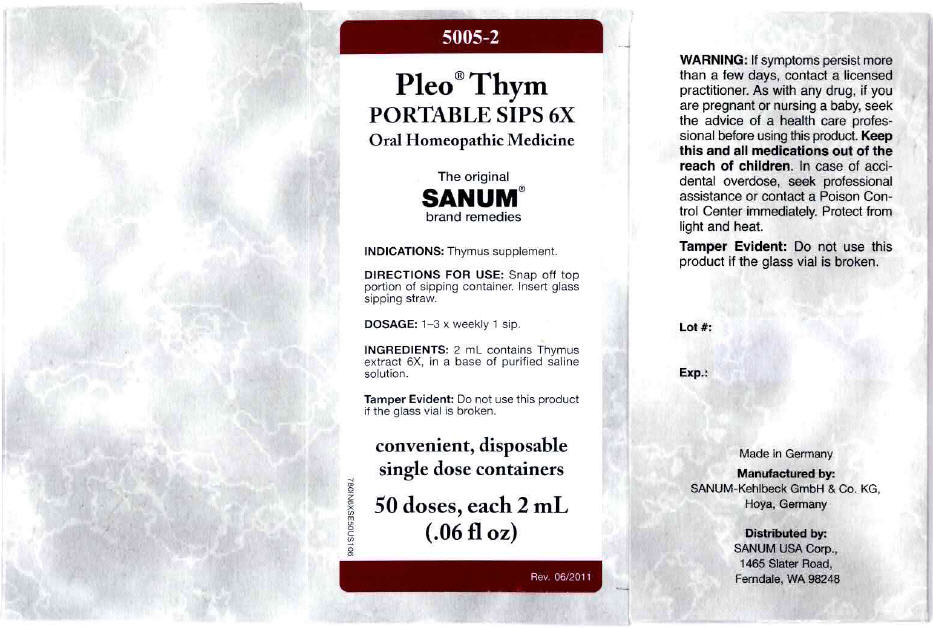 DRUG LABEL: Pleo Thym
NDC: 60681-5005 | Form: LIQUID
Manufacturer: Sanum Kehlbeck GmbH & Co. KG
Category: homeopathic | Type: HUMAN OTC DRUG LABEL
Date: 20120523

ACTIVE INGREDIENTS: BOS TAURUS THYMUS 6 [hp_X]/2 mL
INACTIVE INGREDIENTS: water; sodium chloride

Pleo™ Thym
PORTABLE SIPS 6X

PURPOSE

Oral Homeopathic Medicine

50 doses, each 2 mL
(.06 fl oz)

INDICATIONS

Thymus supplement.

DIRECTIONS FOR USE

Snap off top portion of sipping container. Insert glass sipping straw.

DOSAGE

1–3 × weekly 1 sip.

INGREDIENTS

INACTIVE INGREDIENT

2 mL contains Thymus extract 6X in a base of purified saline solution.

WARNING

If symptoms persist more than a few days, contact a licensed practitioner. As with any drug, if you are pregnant or nursing a baby, seek the advice of a health care professional before using this product.

KEEP OUT OF REACH OF CHILDREN

Keep this and all medications out of the reach of children. In case of accidental overdose, seek professional assistance or contact a Poison Control Center immediately.

STORAGE AND HANDLING

Protect from light and heat.

Tamper Evident

Do not use this product if the glass vial is broken or if imprinted security strip on carton is torn.

Made in Germany

Distributed by:
SANUM USA Corp.
1465 Slater Road
Ferndale, WA 98248

Manufactured By:
Sanum-Kehlbeck GmbH & Co. KG

Rev. 07/2005

PRINCIPAL DISPLAY PANEL - 2 mL Vial Carton

5005-2

Pleo® Thym
PORTABLE SIPS 6X
Oral Homeopathic Medicine

The original
SANUM®
brand remedies

INDICATIONS: Thymus supplement.

DIRECTIONS FOR USE: Snap off top
portion of sipping container. Insert glass
sipping straw.

DOSAGE: 1–3 x weekly 1 sip.

INGREDIENTS: 2 mL contains Thymus
extract 6X, in a base of purified saline
solution.

Tamper Evident: Do not use this product
if the glass vial is broken.

convenient, disposable
single dose containers

50 doses, each 2 mL
(.06 fl oz)

Rev. 06/2011

780IN6XSE50US106